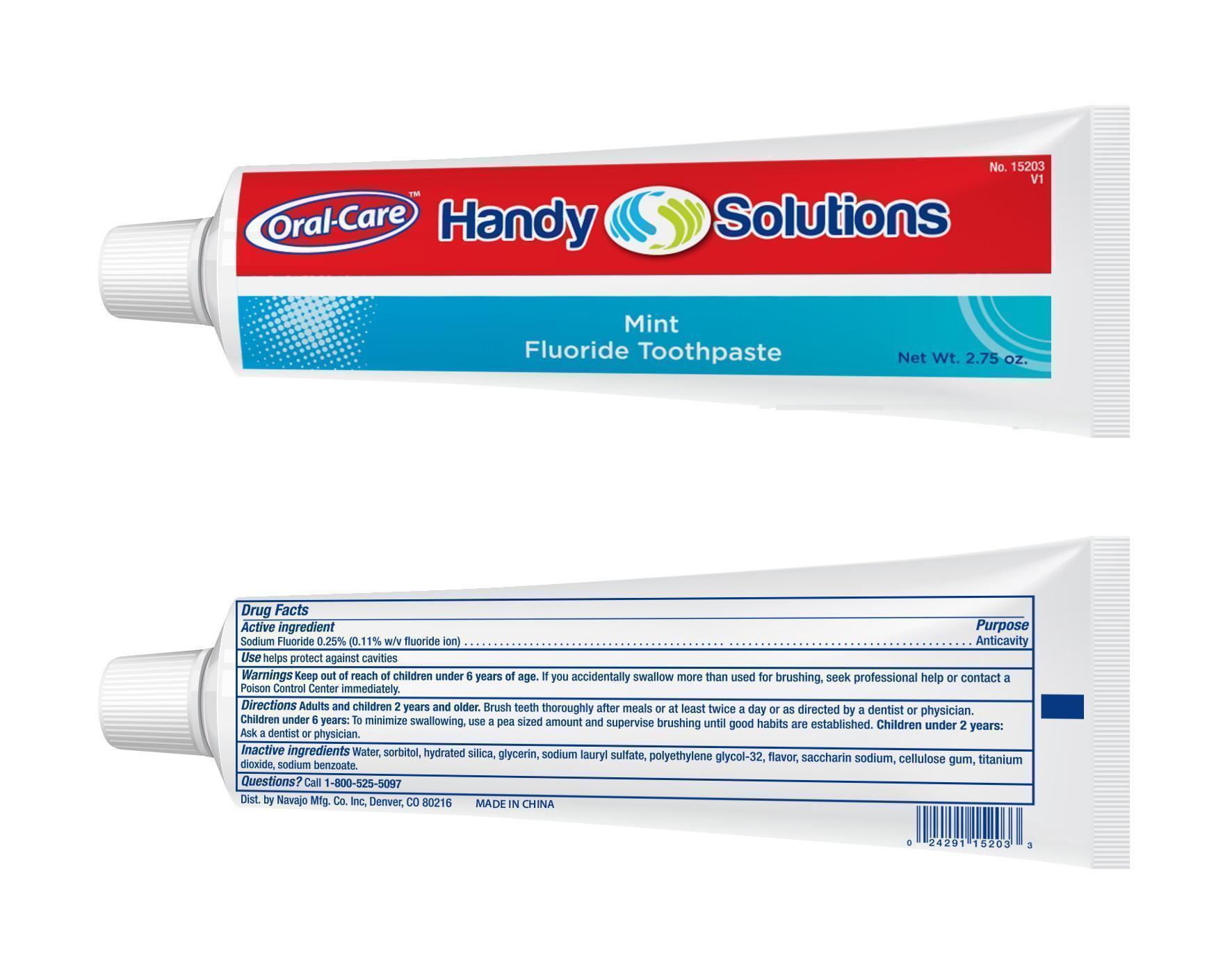 DRUG LABEL: Handy Solutions Mint Fluoride Tooth
NDC: 67751-035 | Form: PASTE
Manufacturer: Navajo Manufacturing Co., Inc.
Category: otc | Type: HUMAN OTC DRUG LABEL
Date: 20150621

ACTIVE INGREDIENTS: SODIUM FLUORIDE 2.5 mg/1 g
INACTIVE INGREDIENTS: WATER; SORBITOL; HYDRATED SILICA; GLYCERIN; SODIUM LAURYL SULFATE; SACCHARIN SODIUM; CARBOXYMETHYLCELLULOSE SODIUM, UNSPECIFIED FORM; SODIUM BENZOATE

Handy Solutions Mint Fluoride Toothpaste

Active ingredient

Sodium Fluoride 0.25%

Purpose

Anticavity

Use

helps protect against cavities

Warnings

Keep out of reach of children under 6 years of age.

If you accidentally swallow more than used for brushing, seek professional help or contact a Poison Control Center Immediately

Directions

Adults and children 2 years and older. Brush teeth thoroughly after meals or at least twice a day or as directed by a dentist or physician. Children under 6 years: To minimize swallowing, use a pea sized amount and supervise brushing until good habits are established. Children under 2 years: Ask a dentist or physician

Inactive ingredients

Water, Sorbitol, Hydrated Silica, Glycerin, Sodium Lauryl Sulfate, Polyethylene Glycol-32, Flavor, Saccharin Sodium, Cellulose Gum, Titanium Dioxide, Sodium Benzoate.

Questions?

Call 1-800-525-5097